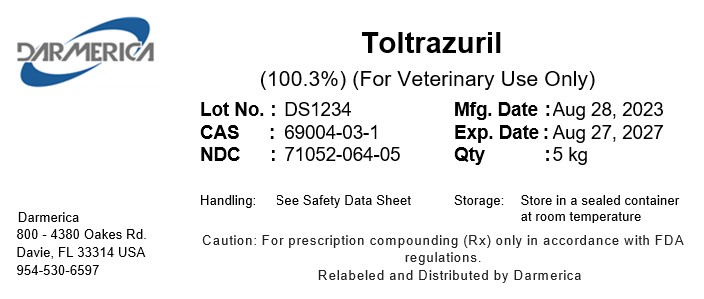 DRUG LABEL: Toltrazuril
NDC: 71052-064 | Form: POWDER
Manufacturer: DARMERICA, LLC
Category: other | Type: BULK INGREDIENT - ANIMAL DRUG
Date: 20260213

ACTIVE INGREDIENTS: Toltrazuril 1 kg/1 kg

Toltrazuril